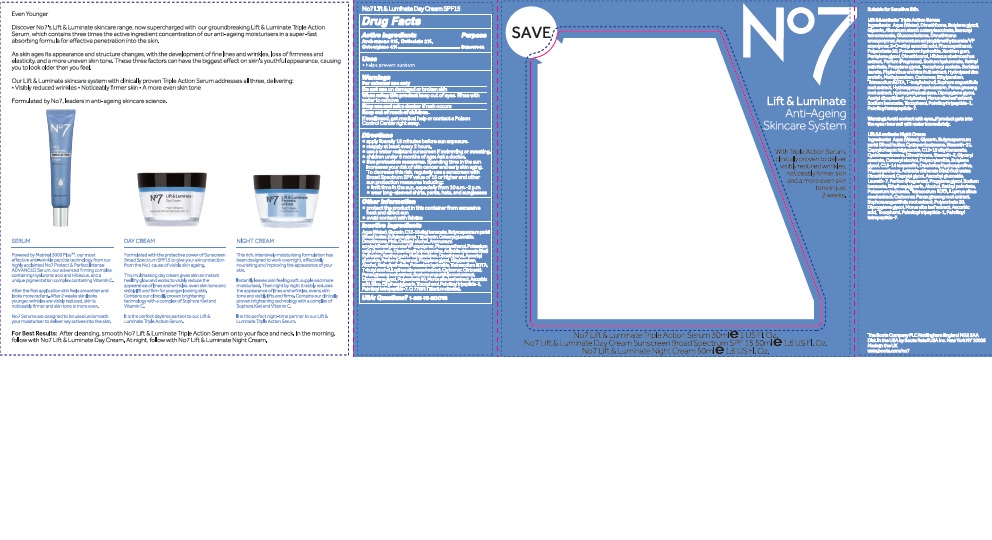 DRUG LABEL: No7 Lift and Luminate Day Cream SPF 15
NDC: 11489-103 | Form: CREAM
Manufacturer: BCM Ltd
Category: otc | Type: HUMAN OTC DRUG LABEL
Date: 20160927

ACTIVE INGREDIENTS: AVOBENZONE 1.5 g/50 g; OCTOCRYLENE 2 g/50 g; OCTISALATE 1 g/50 g
INACTIVE INGREDIENTS: WATER; GLYCERIN; DIMETHICONE; ALKYL (C12-15) BENZOATE; MICA; CETEARYL GLUCOSIDE; TRIBEHENIN; AMMONIUM ACRYLOYLDIMETHYLTAURATE/VP COPOLYMER; PHENOXYETHANOL; DIPALMITOYL HYDROXYPROLINE; ALCOHOL; SHEA BUTTER; POTASSIUM CETYL PHOSPHATE; CITRIC ACID ACETATE; BUTYLENE GLYCOL; METHYLPARABEN; ETHYLPARABEN; XANTHAN GUM; DIPROPYLENE GLYCOL; VITAMIN A PALMITATE; ASCORBYL GLUCOSIDE; EDETATE SODIUM; TERT-BUTYL ALCOHOL; PANAX GINSENG ROOT OIL; LUPINUS ALBUS SEED; POLYSORBATE 20; POTASSIUM HYDROXIDE; ETHYLHEXYLGLYCERIN; TOCOPHEROL; ASCORBIC ACID; TITANIUM DIOXIDE; PALMITOYL TETRAPEPTIDE-7

No7 Lift and Luminate Day Cream SPF 15

Carton Active Ingredients Section

Active ingredients

Avobenzone 3%

Octisalate 2%

Octocrylene 4%

Uses

Uses - helps prevent sunburn

Warnings

For external use only

Do not use on damaged or broken skin

When using this product keep out of eyes. Rinse with water to remove.

Ask a doctor

Stop use and ask a doctor if rash occurs

Keep out of reach of children

If swallowed, get medical help or contact a Poison Control Center right away

Directions

Apply liberally 15 minutes before sun exposure

reapply at least every 2 hours

use a water resistant sunscreen if swimming or sweating

children under 6 months of age: Ask a doctor

Sun Protection Measures. Spending time in the sun increases your risk of skin cancer and early skin aging.

To decrease this risk, regularly use a sunscreen with a Broad Spectrum SPF value of 15 or higher and other sun protection measures including:

Limit time in the sun, especially from 10 a.m - 2 p.m.

wear long-sleeved shirts,pants,hats and sunglasses.

Storage

Other information

Protect the product in this container from excessive heat and direct sun

Avoid contact with fabrics

Inactive ingredients

Aqua(Water), Glycerin, C12-15 alkyl benzoate, Dimethicone, Mica, Cetearyl glucoside, Tribehenin, Butylene glycol, Ammonium acryloydimethyltaurate/VP copolymer, Phenoxyethanol, Dipalmitoyl hydroxyproline, Alcohol, Butyrospermum parkii (Shea) butter, Potassium cetyl phosphate, Actinidia chinensis(Kiwi) fruit water, Cetearyl alcohol, Dimethiconol, Methylparaben, Parfum(Fragrance), Propylene glycol, Xanthan gum, Ethylparaben, Dipropylene glycol, Retinyl palmitate, Ascorbyl glucoside,, Tetrasodium EDTA, T-butyl alcohol, Lupinus albus seed extract, Carbomer, Citric acid, Panax ginseng root extract, Sophora angustifolia root extract,Polysorbate 20, Morus alba leaf extract, Ascorbic acid, Potassium hydroxide, Ethylhexylglycerin, Silica, Tocopherol, Palmitoyl tripeptide-1, Palmitoyl tetrapeptide-7, CI 77891(Titanium dioxide)

Description

Even Younger

Discover No7's Lift and Luminate skincare range, now supercharged with our groundbreaking Lift and Luminate Triple Action Serum, which contains three times the active ingredient concentration of our ant-ageing moisturisers in a super-fast absorbing formula for effective penetration into the skin.

As skin ages its appearance and structure chnages, with the development of fine lines and wrinkles, loss of firmness and elasticity, and a more uneven skin tone. These three factors can have the biggest effect on skin's youthful appearance, causing you to look older than you feel.

Our Lift and Luminate skincare system with clinically proven Triple Action Serum addresses all three, delivering: Visibly reduced wrinkles. Noticably firmer skin. A more even skin tone.

Description

SERUM

Powered by Matrixyl 3000 Plus TM, our most effective anti-wrinkle peptide technology from our highly acclaimed No7 Protect and Perfect Intense Advanced Serum, our advanced firming complex containing Hyaluronic acid and Hibiscus, and a unique pigmentation complex containing Vitamin C.

After the first application skin feels smoother and looks more radiant. After 2 weeks skin looks younger, wrinkles are visibly reduced, skin is noticeably firmer and skin tone is more even.

No7 Serums are designed to be used underneath your moisturiser to deliver key actives into the skin.

DAY CREAM

Formulated with the protective power of Sunscreen Broad Spectrum SPF 15 to give your skin protection from the No 1 cause of vsible skin ageing.

This multitasking day cream gives skin an instant healthy glow and works to visibly reduce the appearance of lines and wrinkles, even skin tone and visibly lift and firm for younger looking skin. Contains our clinically proven brightening technology with a complex of Sophora Kiwi and Vitamin C.

It is the perfect daytime partner to our Lift and Luminate Triple Action Serum.

NIGHT CREAM

PATIENT COUNSELING INFORMATION

The Boots Company PLC Nottingham England NG2 3AA

Dist. by Boots Retail USA Inc. New York NY1005

Made in the UK

www.boots.com/no7